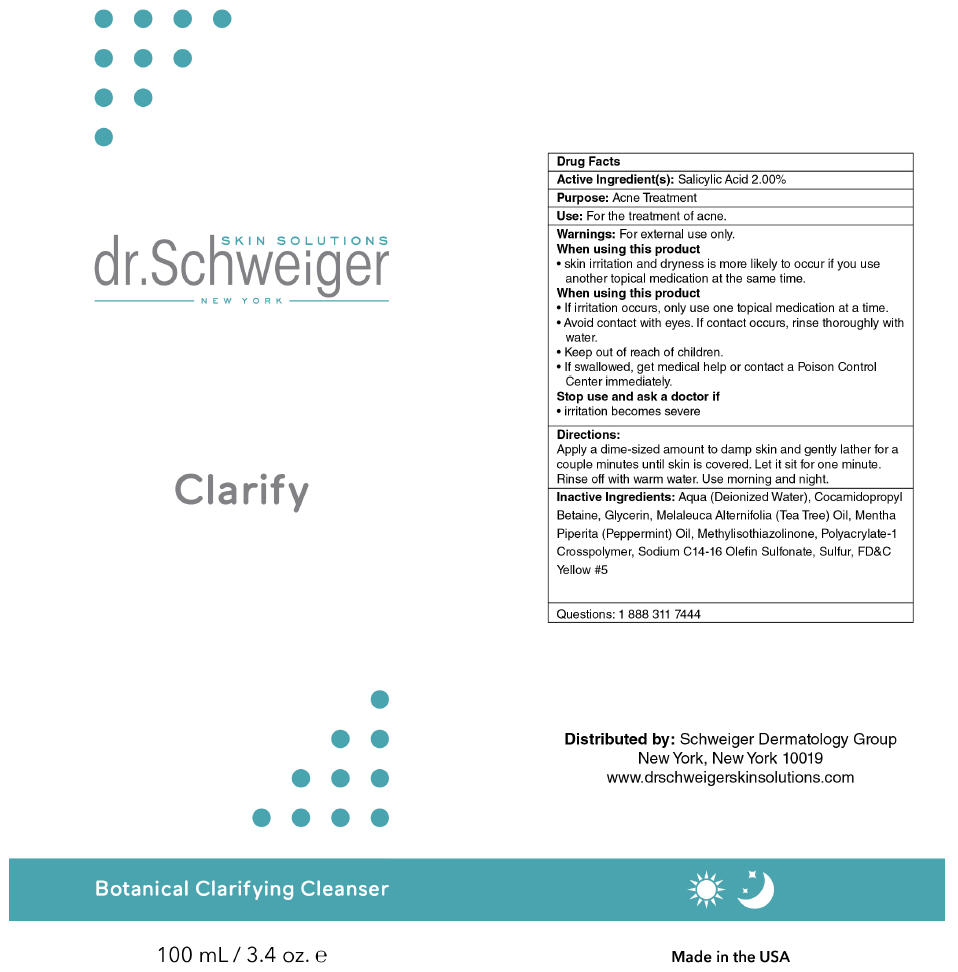 DRUG LABEL: CLARIFY 
NDC: 70911-114 | Form: GEL
Manufacturer: SCHWEIGER DERMATOLOGY GROUP
Category: otc | Type: HUMAN OTC DRUG LABEL
Date: 20160914

ACTIVE INGREDIENTS: SALICYLIC ACID 20 mg/1 mL
INACTIVE INGREDIENTS: WATER; GLYCERIN; Cocamidopropyl Betaine; Melaleuca Alternifolia Leaf; Peppermint Oil; Methylisothiazolinone; Sodium C14-16 Olefin Sulfonate; Sulfur; FD&C Yellow NO. 5

CLARIFY
BOTANICAL CLARIFYING WASH

Drug Facts

Active ingredients

Salicylic Acid 2.00%

Purpose

Acne Treatment

Uses

For the treatment of acne.

Warnings

For External use only.

When using this product skin irritation and dryness is more likely to occur if you use another topical acne medication at the same time. If irritation occurs, use only one topical medication at a time.

- Keep out of reach of children
- When using this product, rinse immediately with water if it gets in eyes.
- If swallowed, consult a physician or poison control center.

Directions

- Wet face. Apply to hands, add water and work into lather. Gently massage all over face being careful to avoid the eyes.
- Rinse thoroughly and pat dry.
- Use daily for best results.

Additional Information

Store at room temperature.

Inactive ingredients

Aqua (Deionized Water), Cocamidopropyl Betaine, Glycerin, Melaleuca Alternifolia (Tea Tree) Oil, Mentha Piperita (Peppermint) Oil, Methylisothiazolinone, Polycrylate-1 Crosspolymer, Sodium C14-16 Olefin Sulfonate, Sulfur, FD&C Yellow #5.

Questions

1 888 311 7444

Distributed by: Schweiger Dermatology Group
NY, NY 10019

PRINCIPAL DISPLAY PANEL - 100 mL Bottle Label

SKIN SOLUTIONS
dr.Schweiger
NEW YORK

Clarify

Botanical Clarifying Cleanser

100 mL / 3.4 oz. e